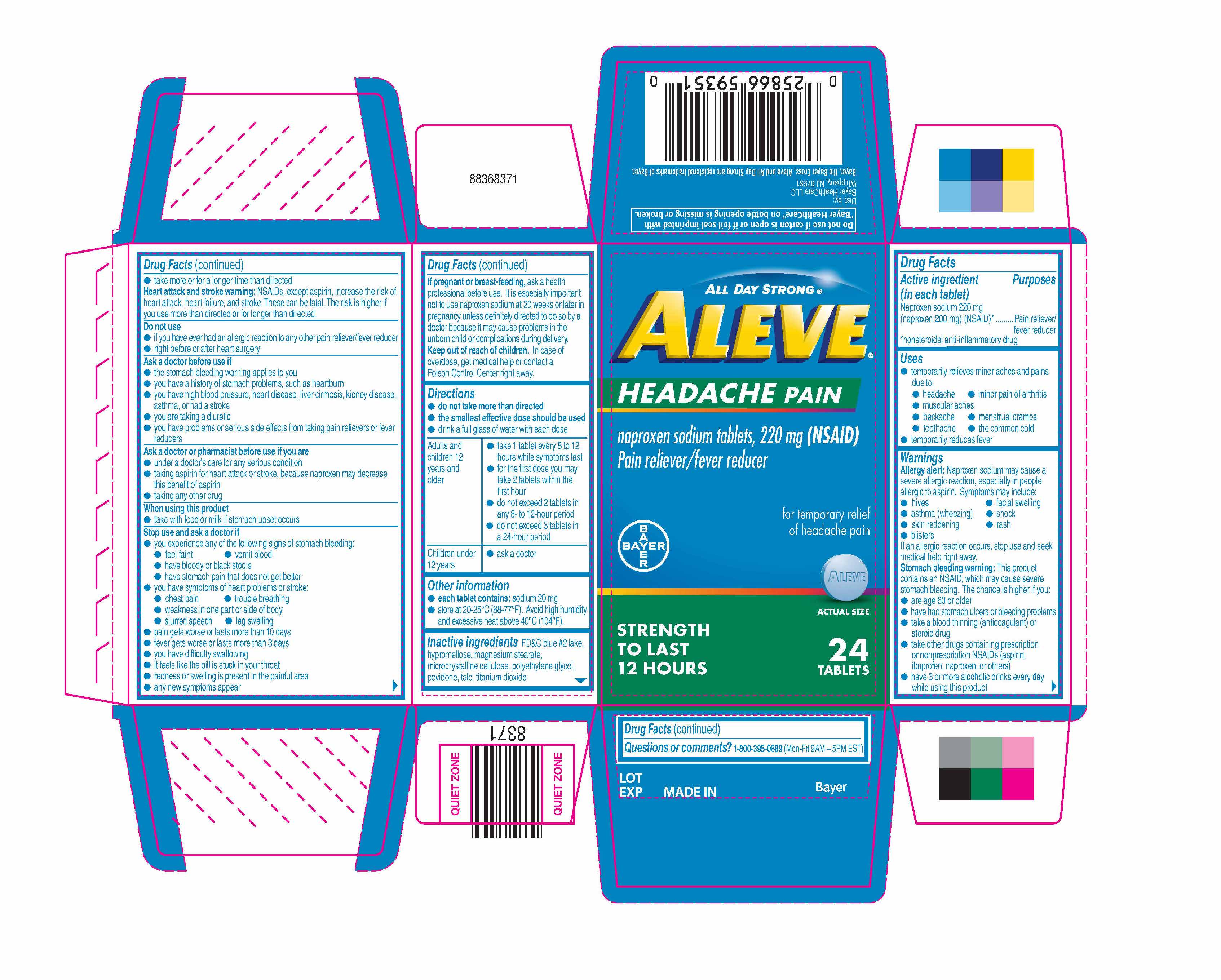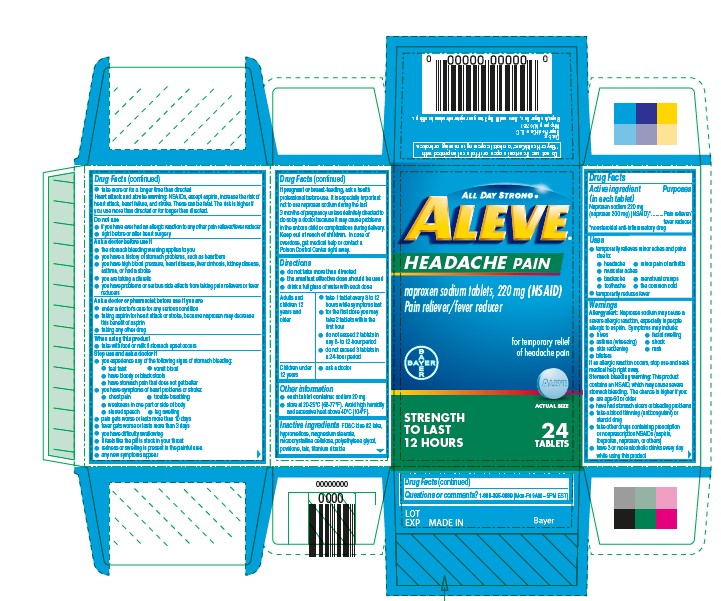 DRUG LABEL: Aleve Headache Pain
NDC: 0280-0041 | Form: TABLET
Manufacturer: Bayer HealthCare LLC
Category: otc | Type: HUMAN OTC DRUG LABEL
Date: 20251204

ACTIVE INGREDIENTS: NAPROXEN SODIUM 220 mg/1 1
INACTIVE INGREDIENTS: TITANIUM DIOXIDE; FD&C BLUE NO. 2; TALC; POLYETHYLENE GLYCOL, UNSPECIFIED; POVIDONE; HYPROMELLOSES; MAGNESIUM STEARATE; CELLULOSE, MICROCRYSTALLINE

Aleve ® Headache Pain

Active Ingredient

Naproxen Sodium 220mg

Purposes:

Pain reliever/fever reducer

Uses:

- temporarily relieves minor aches and pains due to:
  - headache
  - minor pain of arthritis
  - muscular aches
  - backache
  - menstrual cramps
  - toothache
  - the common cold
- temporarily reduces fever

Warnings:

Allergy Alert: Naproxen sodium may cause a severe allergic reaction, especially in people allergic to aspirin. Symptoms may include:

- hives
- facial swelling
- asthma (wheezing)
- shock
- skin reddening
- rash
- blisters

If an allergic reaction occurs, stop use and seek medical help right away.

Stomach bleeding warning: This product contains an NSAID, which may cause severe stomach bleeding. The chance is higher if you:

- are age 60 or older
- have had stomach ulcers or bleeding problems
- take a blood thinning (anticoagulant) or steroid drug
- take other drugs containing prescription or nonprescription NSAIDs (aspirin, ibuprofen, naproxen, or others)
- have 3 or more alcoholic drinks every day while using this product
- take more or for a longer time than directed

Heart attack and stroke warning: NSAIDs, except aspirin, increase the risk of heart attack, heart failure, and stroke. These can be fatal. The risk is higher if you use more than directed or for longer than directed.

Do Not Use:

- if you have ever had an allergic reaction to any other pain reliever/fever reducer
- right before or after heart surgery

Ask a Doctor:

- the stomach bleeding warning applies to you
- you have a history of stomach problems, such as heartburn
- you have high blood pressure, heart disease, liver cirrhosis, kidney disease, asthma, or had a stroke
- you are taking a diuretic
- you have problems or serious side effects from taking pain relievers or fever reducers

Ask a doctor or pharmacist before use

- under a doctor's care for any serious condition
- taking aspirin for heart attack or stroke, because naproxen may decrease this benefit of aspirin
- taking any other drug

When using this product

- take with food or milk if stomach upset occurs

Stop use and ask a doctor

- you experience any of the following signs of stomach bleeding:
  - feel faint
  - vomit blood
  - have bloody or black stools
  - have stomach pain that does not get better
- you have symptoms of heart problems or stroke:
  - chest pain
  - trouble breathing
  - weakness in one part or side of body
  - slurred speech
  - leg swelling
- pain gets worse or lasts more than 10 days
- fever gets worse or lasts more than 3 days
- you have difficulty swallowing
- it feels like the pill is stuck in your throat
- redness or swelling is present in the painful area
- any new symptoms appear

The pregnancy/breast-feeding warning:

If pregnant or breast-feeding, ask a health professional before use. It is especially important not to use naproxen sodium at 20 weks or later in pregnancy unless definitely directed to do so by a doctor because it may cause problems in the unborn child or complications during delivery.

Keep out of reach of children. In case of overdose, get medical help or contact a Poison Control Center right away.

Directions:

- do not take more than directed
- the smallest effective dose should be used
- drink a full glass of water with each dose

Adults and children 12 years and older | - take 1 tablet every 8 to 12 hours while symptoms last - for the first dose you may take 2 tablets within the first hour - do not exceed 2 tablets in any 8- to 12-hour period - do not exceed 3 tablets in a 24-hour period
Children under 12 years | - ask a doctor

Other information:

- each tablet contains: sodium 20 mg
- store at 20-25 ° C (68-77 ° F). Avoid high humidity and excessive heat above 40 ° C (104 ° F).

Inactive ingredient

FD&C BLUE #2 LAKE, HYPROMELLOSE, MAGNESIUM STEARATE, MICROCRYSTALLINE CELLULOSE, POLYETHYLENE GLYCOL, POVIDONE, TALC, TITANIUM DIOXIDE

Questions & comments:

1-800-395-0689 (Mon-Fri 9AM-5PM EST)

Dist. by :

Bayer Healthcare LLC

Whippany, NJ 07981

PACKAGE LABEL PRINCIPAL DISPLAY PANEL - 24 Count Tablets

ALL DAY STRONG®

ALEVE

HEADACHE PAIN

naproxen sodium tablets, 220 mg (NSAID)

Pain reliever/fever reducer

Bayer

For temporary relief of headache pain

ACTUAL SIZE

STRENGTH TO LAST 12 HOURS

TABLETS